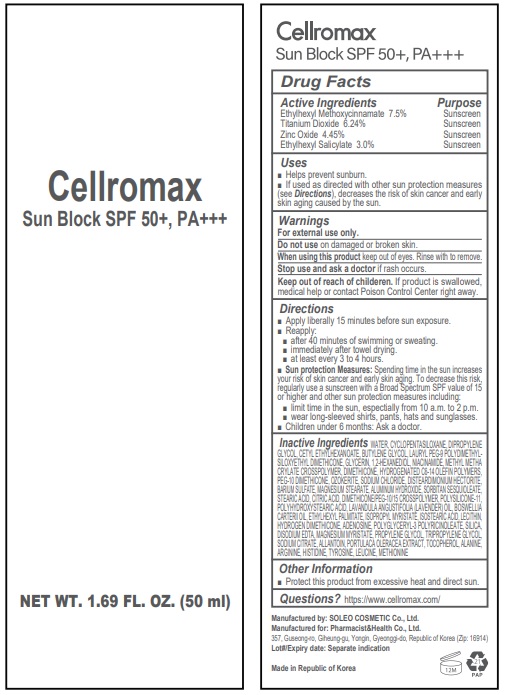 DRUG LABEL: Cellromax Sun Block
NDC: 79895-104 | Form: CREAM
Manufacturer: Pharmacist&Health Co., Ltd.
Category: otc | Type: HUMAN OTC DRUG LABEL
Date: 20201116

ACTIVE INGREDIENTS: ZINC OXIDE 4.455 g/100 mL; TITANIUM DIOXIDE 6.24 g/100 mL; OCTINOXATE 7.5 g/100 mL; OCTISALATE 3 g/100 mL
INACTIVE INGREDIENTS: DIMETHICONE; PEG-10 DIMETHICONE (600 CST); SODIUM CHLORIDE; SORBITAN SESQUIOLEATE; POLYHYDROXYSTEARIC ACID (2300 MW); FRANKINCENSE OIL; ISOSTEARIC ACID; HYDROGEN DIMETHICONE (13 CST); ADENOSINE; SILICON DIOXIDE; TRIPROPYLENE GLYCOL; SODIUM CITRATE; ALLANTOIN; TOCOPHEROL; ARGININE; BUTYLENE GLYCOL; GLYCERIN; 1,2-HEXANEDIOL; NIACINAMIDE; METHYL METHACRYLATE/GLYCOL DIMETHACRYLATE CROSSPOLYMER; HYDROGENATED POLY(C6-14 OLEFIN; 2 CST); CERESIN; DISTEARDIMONIUM HECTORITE; BARIUM SULFATE; ALUMINUM HYDROXIDE; CITRIC ACID MONOHYDRATE; DIMETHICONE/PEG-10/15 CROSSPOLYMER; DIMETHICONE/VINYL DIMETHICONE CROSSPOLYMER (SOFT PARTICLE); LAVENDER OIL; ETHYLHEXYL PALMITATE; ISOPROPYL MYRISTATE; LECITHIN, SOYBEAN; PROPYLENE GLYCOL; ALANINE; HISTIDINE; LEUCINE; MAGNESIUM STEARATE; POLYGLYCERYL-3 PENTARICINOLEATE; STEARIC ACID; MAGNESIUM MYRISTATE; WATER; DIPROPYLENE GLYCOL; CYCLOMETHICONE 5; CETYL ETHYLHEXANOATE; METHIONINE; PORTULACA OLERACEA LEAF; LAURYL PEG-9 POLYDIMETHYLSILOXYETHYL DIMETHICONE; TYROSINE; EDETATE DISODIUM

ACTIVE INGREDIENT

Ethylhexyl Methoxycinnamate 7.5%, Titanium Dioxide 6.24%, Zinc Oxide 4.455%, Ethylhexyl Salicylate3.0%

INACTIVE INGREDIENT

Water, Cyclopentasiloxane, Dipropylene Glycol, Cetyl Ethylhexanoate, Butylene Glycol, Lauryl PEG-9 Polydimethylsiloxyethyl Dimethicone, Glycerin, 1,2-Hexanediol, Niacinamide, Methyl Methacrylate Crosspolymer, Dimethicone, Hydrogenated C6-14 Olefin Polymers, PEG-10 Dimethicone, Ozokerite, Sodium Chloride, Disteardimonium Hectorite, Barium Sulfate, Magnesium Stearate, Aluminum Hydroxide, Sorbitan Sesquioleate, Stearic Acid, Citric Acid, Dimethicone/PEG-10/15 Crosspolymer, Polysilicone-11, Polyhydroxystearic Acid, Lavandula Angustifolia (Lavender) Oil, Boswellia Carterii Oil, Ethylhexyl Palmitate, Isopropyl Myristate, Isostearic Acid, Lecithin, Hydrogen Dimethicone, Adenosine, Polyglyceryl-3 Polyricinoleate, Silica, Disodium EDTA, Magnesium Myristate, Propylene Glycol, Tripropylene Glycol, Sodium Citrate, Allantoin, Portulaca Oleracea Extract, Tocopherol, Alanine, Arginine, Histidine, Tyrosine, Leucine, Methionine

Purpose: Sunscreen

DESCRIPTION

Directions: 1. Apply after basic skin care product. 2. Spread an appropriate amount over the entire face following the skin texture. 3. Reapply as required.

Do not use on damaged or broken Skin. Stop use and ask a doctor if rash occurs.

Keep Out of Reach of Children.

WARNINGS

For external use only.

DOSAGE AND ADMINISTRATION

Apply appropriate amount on your skin.

INDICATIONS AND USAGE

Apply with your skin before direct sunlight.